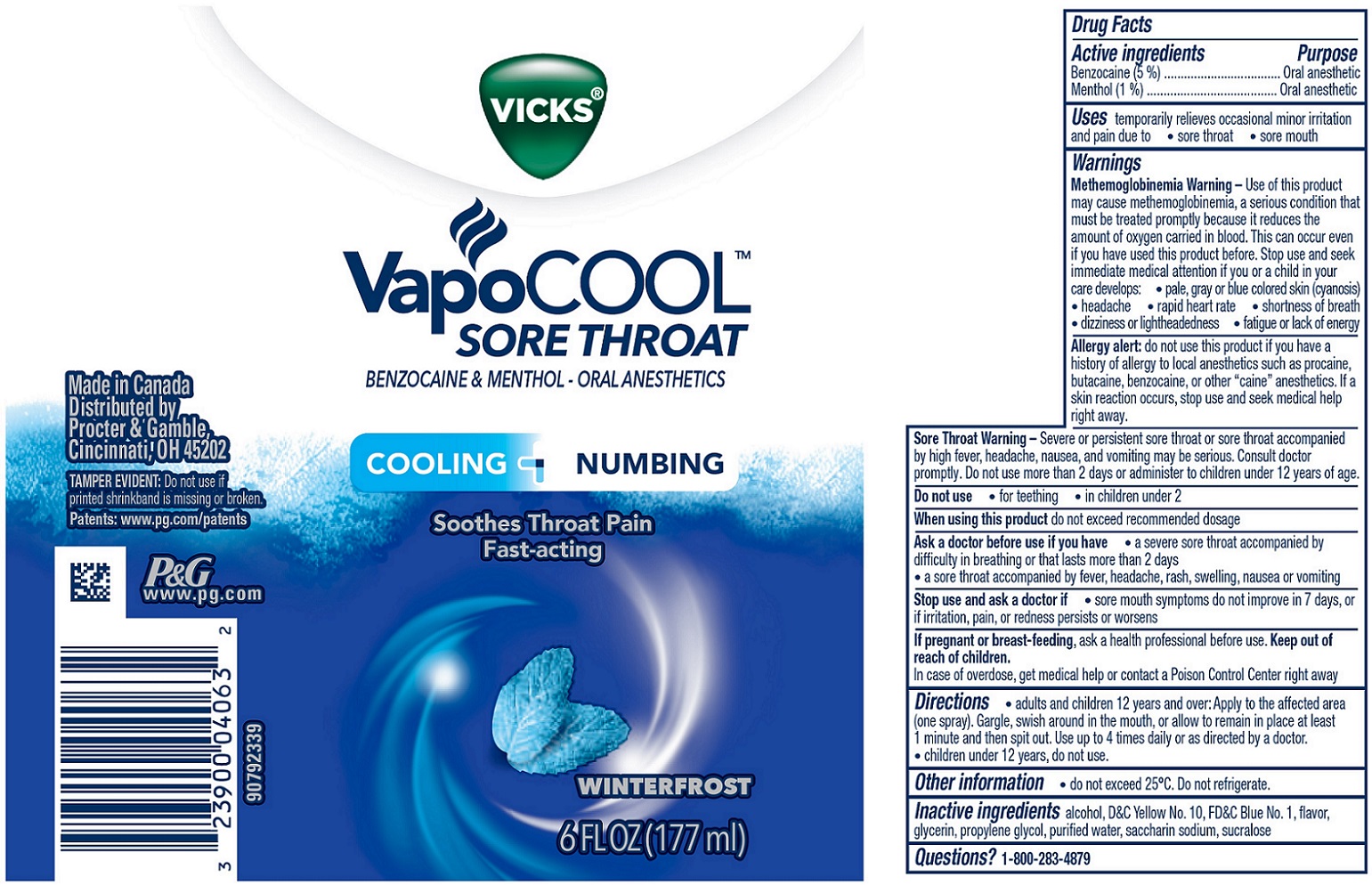 DRUG LABEL: Vicks VapoCool
NDC: 37000-928 | Form: LIQUID
Manufacturer: The Procter & Gamble Manufacturing Company
Category: otc | Type: HUMAN OTC DRUG LABEL
Date: 20251006

ACTIVE INGREDIENTS: BENZOCAINE 5 g/100 mL; MENTHOL 1 g/100 mL
INACTIVE INGREDIENTS: GLYCERIN; ALCOHOL; D&C YELLOW NO. 10; SUCRALOSE; FD&C BLUE NO. 1; PROPYLENE GLYCOL; WATER; SACCHARIN SODIUM

VICKS VAPOCOOL SORE THROAT BENZOCAINE & MENTHOL - ORAL ANESTHETICS Spray

Drug Facts

Active ingredients

Benzocaine (5 %)
Menthol (1 %)

Purpose

Oral anesthetic

Oral anesthetic

Uses

temporarily relieves occasional minor irritation and pain due to

- sore throat
- sore mouth

Warnings

Methemoglobinemia Warning–

Use of this product may cause methemoglobinemia, a serious condition that must be treated promptly because it reduces the amount of oxygen carried in blood. This can occur even if you have used this product before. Stop use and seek immediate medical attention if you or a child in your care develops:

- pale, gray or blue colored skin (cyanosis)
- headache
- rapid heart rate
- shortness of breath
- dizziness or lightheadedness
- fatigue or lack of energy

Allergy alert:

do not use this product if you have a history of allergy to local anesthetics such as procaine, butacaine, benzocaine, or other “caine” anesthetics. If a skin reaction occurs, stop use and seek medical help right away.

Sore Throat Warning –

Severe or persistent sore throat or sore throat accompanied by high fever, headache, nausea, and vomiting may be serious. Consult doctor promptly. Do not use more than 2 days or administer to children under 12 years of age.

Do not use

- for teething
- in children under 2

When using this product

do not exceed recommended dosage

Ask a doctor before use if you have

- a severe sore throat accompanied by difficulty in breathing or that lasts more than 2 days
- a sore throat accompanied by fever, headache, rash, swelling, nausea or vomiting

Stop use and ask a doctor if

- sore mouth symptoms do not improve in 7 days, or if irritation, pain, or redness persists or worsens

If pregnant or breast-feeding,

ask a health professional before use.

Keep out of reach of children.

OVERDOSAGE

In case of overdose, get medical help or contact a Poison Control Center right away.

Directions

- adults and children 12 years and over: Apply to the affected area (one spray). Gargle, swish around in the mouth, or allow to remain in place at least 1 minute and then spit out. Use up to 4 times daily or as directed by a doctor.
- children under 12 years, do not use.

Other information

- do not exceed 25ºC. Do not refrigerate.

Inactive ingredients

alcohol, D&C Yellow No. 10, FD&C Blue No. 1, flavor, glycerin, propylene glycol, purified water, saccharin sodium, sucralose

Questions?

1-800-283-4879

TAMPER EVIDENT: Do not use if printed shrinkband is missing or broken.

Made in Canada
Distributed by
Procter & Gamble,
Cincinnati, OH 45202

PRINCIPAL DISPLAY PANEL - 177 ml Bottle Label

VICKS®

VapoCOOL

SORE THROAT

BENZOCAINE & MENTHOL - ORAL ANESTHETICS

COOLING + NUMBING

Soothes Throat Pain
Fast-acting

WINTERFROST

6 FL OZ (177 ml)